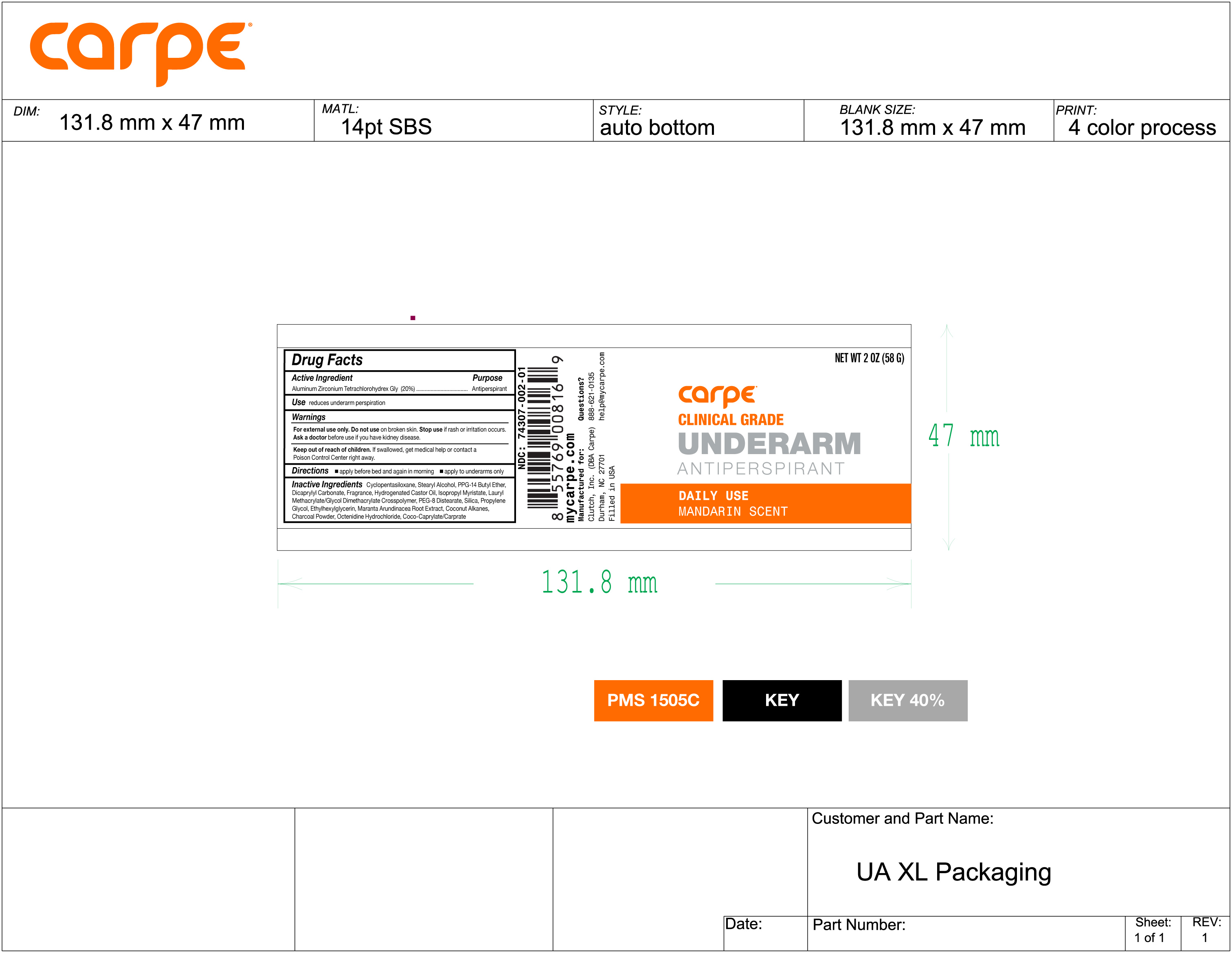 DRUG LABEL: Underarm Antiperspirant Daily Use Mandarin Scent
NDC: 74307-002 | Form: STICK
Manufacturer: Clutch Inc
Category: otc | Type: HUMAN OTC DRUG LABEL
Date: 20251211

ACTIVE INGREDIENTS: ALUMINUM ZIRCONIUM TETRACHLOROHYDREX GLY 20 g/100 g
INACTIVE INGREDIENTS: ETHYLHEXYLGLYCERIN; PPG-14 BUTYL ETHER; COCO-CAPRYLATE/CAPRATE; ISOPROPYL MYRISTATE; LAURYL METHACRYLATE/GLYCOL DIMETHACRYLATE CROSSPOLYMER; CYCLOMETHICONE 5; MARANTA ARUNDINACEA ROOT; OCTENIDINE HYDROCHLORIDE; PROPYLENE GLYCOL; DICAPRYLYL CARBONATE; HYDROGENATED CASTOR OIL; PEG-8 DISTEARATE; COCONUT ALKANES; ACTIVATED CHARCOAL; SILICON DIOXIDE; STEARYL ALCOHOL

Underarm Antiperspirant Daily Use Mandarin Scent

Active Ingredient Purpose

Aluminum Zirconium Tetrachlorohydrex Gly (20%) Antiperspirant

Use

reduces underarm perspiration

KEEP OUT OF REACH OF CHILDREN

Keep out reach of children.If swallowed get medical help or contact a Poison Control Center right away

INDICATIONS AND USAGE

Stop useif rash or irritation occurs.

Warnings

For external use only. Do not useon broken skin. Ask a doctorbefore use if you have kidney disease.

Directions

apply before bed and again in morning

apply to underarm only

Inactive Ingredients
Cyclopentasiloxane, Stearyl Alcohol, PPG-14 Butyl Ether, Dicaprylyl Carbonate, Fragrance, Hydrogenated Castor Oil,
Isopropyl Myristate, Lauryl Methacrylate/Glycol Dimethacrylate Crosspolymer, PEG-8 Distearate, Silica, Propylene Glycol, Ethylhexylglycerin, Maranta Arundinacea Root Extract, Coconut Alkanes, Charcoal Powder, Octenidine Hydrochloride, Coco-Caprylate/Caprate.

PACKAGE LABEL

Underarm Antiperspirant

Daily Use Mandarin Scent

Net Wt 2 OZ 58 G